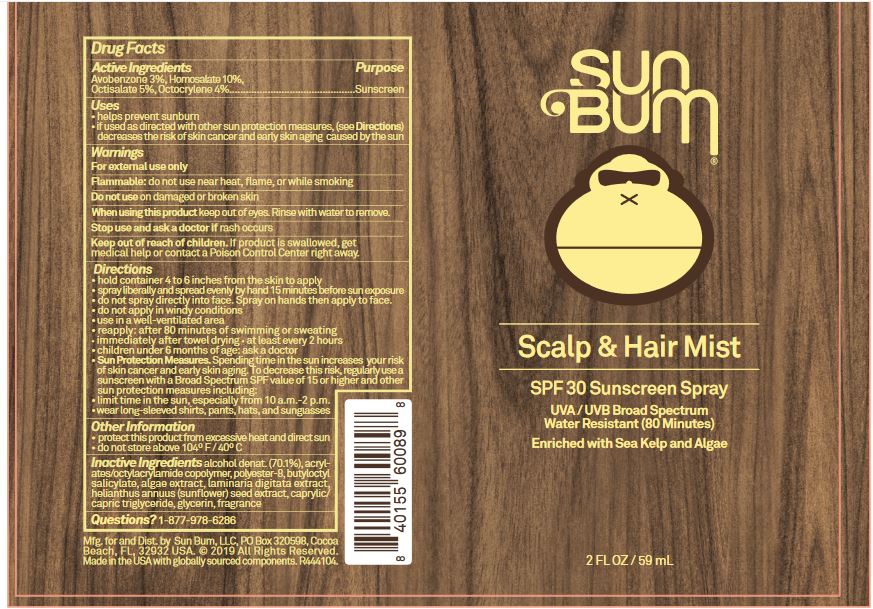 DRUG LABEL: SPF 30 Scalp and Hair Mist
NDC: 69039-280 | Form: SPRAY
Manufacturer: Sun Bum LLC
Category: otc | Type: HUMAN OTC DRUG LABEL
Date: 20220425

ACTIVE INGREDIENTS: AVOBENZONE 30 mg/1 mL; HOMOSALATE 100 mg/1 mL; OCTISALATE 50 mg/1 mL; OCTOCRYLENE 40 mg/1 mL
INACTIVE INGREDIENTS: WATER

SPF 30 Scalp and Hair Mist

Active ingredient

Avobenzone 3%, Homosalate 10%,

Octisalate 5%, Octocrylene 4%

Purpose

Sunscreen

Warnings

For external use only

Flammable: do you not use near heat, flame, or while smoking

Do not use

on damaged or broken skin

Stop use and ask a doctor

if rash occurs.

Keep out of reach of children.

If swallowed, get medical help or contact a Poison Control Center immediately.

Directions

- hold container 4 to 6 inches from scalp and skin to apply
- spray liberally and spread evenly by hand 15 minutes before sun exposure.
- do not spray directly into face. Spray on hands then apply to face and hairline.
- do not apply in windy conditions
- use in well ventilated area
- reapply: after 80 minutes of swimming or sweating
- immediately after towel drying
- at least every 2 hours
- children under 6 months of age: ask a doctor

• Sun Protection Measures. Spending time in the sun increases your risk of skin cancer and early skin aging. To decrease this risk, regularly use a sunscreen with a Broad Spectrum SPF value of 15 or higher and other sun protection measures including:

• limit time in the sun, especially from 10 a.m.-2 p.m.

• wear long-sleeved shirts, pants, hats, and sunglasses

Other information

• protect this product from excessive heat and direct sun. Do not store above 104°F/40°C.

Inactive ingredients

water

Questions?

call 1-877-978-6286